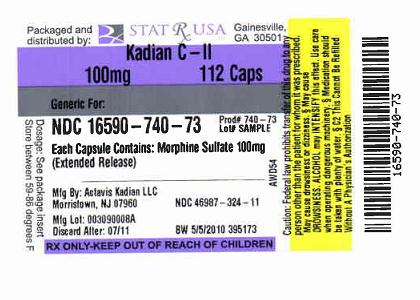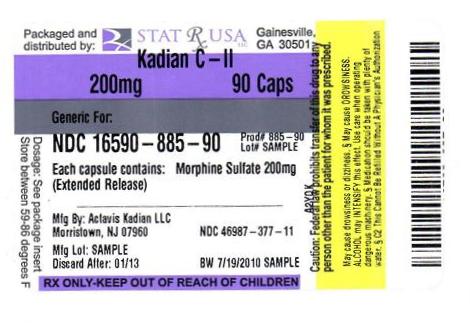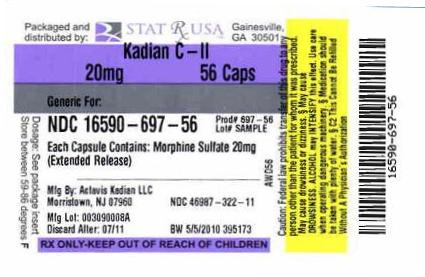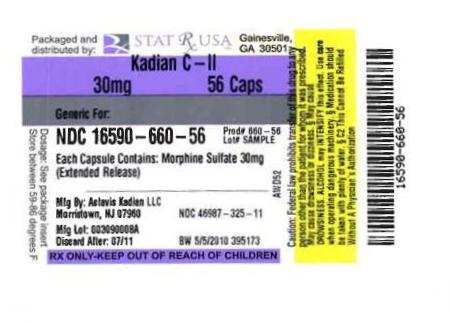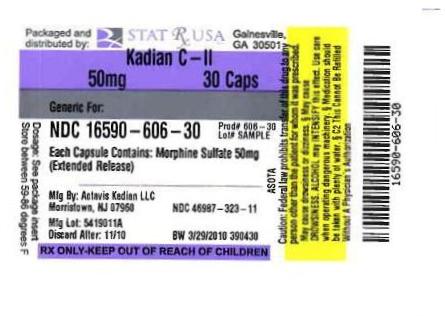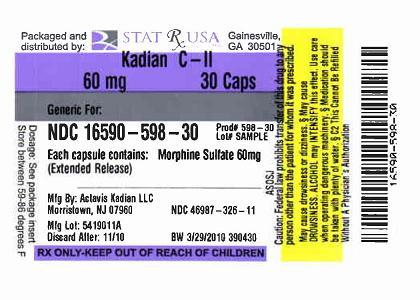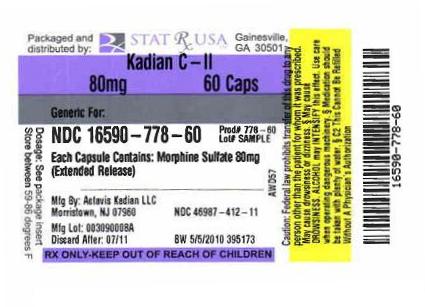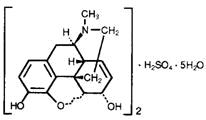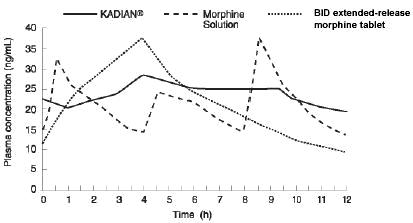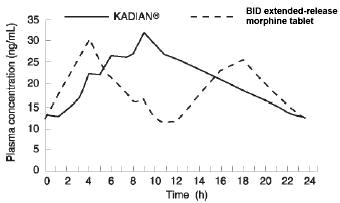 DRUG LABEL: KADIAN
NDC: 16590-697 | Form: CAPSULE, EXTENDED RELEASE
Manufacturer: STAT RX USA LLC
Category: prescription | Type: HUMAN PRESCRIPTION DRUG LABEL
Date: 20110615
DEA Schedule: CII

ACTIVE INGREDIENTS: MORPHINE SULFATE 20 mg/1 1
INACTIVE INGREDIENTS: HYPROMELLOSES; ETHYLCELLULOSES; METHACRYLIC ACID - METHYL METHACRYLATE COPOLYMER (1:1); POLYETHYLENE GLYCOL; DIETHYL PHTHALATE; TALC; STARCH, CORN; SUCROSE; GELATIN; SILICON DIOXIDE; SODIUM LAURYL SULFATE; TITANIUM DIOXIDE; D&C YELLOW NO. 10

40-9101

KADIAN® CII

(morphine sulfate extended-release) Capsules

Revised – February 2010

KADIAN® 10 mg Capsules

KADIAN® 20 mg Capsules

KADIAN® 30 mg Capsules

KADIAN® 50 mg Capsules

KADIAN® 60 mg Capsules

KADIAN® 80 mg Capsules

KADIAN® 100 mg Capsules

KADIAN® 200 mg Capsules

Rx only

BOXED WARNING

KADIAN® contains morphine sulfate, an opioid agonist and a Schedule II controlled substance, with an abuse liability similar to other opioid analgesics. KADIAN® can be abused in a manner similar to other opioid agonists, legal or illicit. This should be considered when prescribing or dispensing KADIAN® in situations where the physician or pharmacist is concerned about an increased risk of misuse, abuse or diversion.

KADIAN® capsules are an extended-release oral formulation of morphine sulfate indicated for the management of moderate to severe pain when a continuous, around-the-clock opioid analgesic is needed for an extended period of time.

KADIAN® Capsules are NOT for use as a prn analgesic.

KADIAN® 100 mg and 200 mg Capsules ARE FOR USE IN OPIOID-TOLERANT PATIENTS ONLY. Ingestion of these capsules or of the pellets within the capsules may cause fatal respiratory depression when administered to patients not already tolerant to high doses of opioids. KADIAN® CAPSULES ARE TO BE SWALLOWED WHOLE OR THE CONTENTS OF THE CAPSULES SPRINKLED ON APPLE SAUCE. THE PELLETS IN THE CAPSULES ARE NOT TO BE CHEWED, CRUSHED, OR DISSOLVED DUE TO THE RISK OF RAPID RELEASE AND ABSORPTION OF A POTENTIALLY FATAL DOSE OF MORPHINE.

DESCRIPTION

KADIAN® (morphine sulfate) capsules are an opioid analgesic supplied in 10 mg, 20 mg, 30 mg, 50 mg, 60 mg, 80 mg, 100 mg, and 200 mg strengths for oral administration.

Chemically, morphine sulfate is 7,8-didehydro-4,5 α-epoxy-17-methyl-morphinan-3,6 α-diol sulfate (2:1) (salt) pentahydrate and has the following structural formula:

Morphine sulfate is an odorless, white, crystalline powder with a bitter taste and a molecular weight of 758 (as the sulfate). It has a solubility of 1 in 21 parts of water and 1 in 1000 parts of alcohol, but is practically insoluble in chloroform or ether. The octanol: water partition coefficient of morphine is 1.42 at physiologic pH and the pKb is 7.9 for the tertiary nitrogen (mostly ionized at pH 7.4).

Each KADIAN® extended-release capsule contains either 10 mg, 20 mg, 30 mg, 50 mg, 60 mg, 80 mg, 100 mg, or 200 mg of Morphine Sulfate USP and the following inactive ingredients common to all strengths: hypromellose, ethylcellulose, methacrylic acid copolymer, polyethylene glycol, diethyl phthalate, talc, corn starch, and sucrose. The capsule shells contain gelatin, silicon dioxide, sodium lauryl sulfate, titanium dioxide, and black ink, D and C red #28, FD and C blue #1 (10 mg), D and C yellow #10 (20 mg), FD and C red #3, FD and C blue #1 (30 mg), D and C red #28, FD and C red #40, FD and C blue #1 (50 mg), D and C red #28, FD and C red #40, FD and C blue #1 (60 mg), FD and C blue #1, FD and C red #40, FD and C yellow #6 (80 mg), D and C yellow #10, FD and C blue #1 (100 mg), black iron oxide, yellow iron oxide, red iron oxide (200 mg).

CLINICAL PHARMACOLOGY

Morphine is a natural product that is the prototype for the class of natural and synthetic opioid analgesics. Opioids produce a wide spectrum of pharmacologic effects including analgesia, dysphoria, euphoria, somnolence, respiratory depression, diminished gastrointestinal motility, altered circulatory dynamics, histamine release and physical dependence.

Morphine produces both its therapeutic and its adverse effects by interaction with one or more classes of specific opioid receptors located throughout the body. Morphine acts as a pure agonist, binding with and activating opioid receptors at sites in the peri-aqueductal and peri-ventricular grey matter, the ventro-medial medulla and the spinal cord to produce analgesia.

Effects on the Central Nervous System

The principal actions of therapeutic value of morphine are analgesia and sedation (i.e., sleepiness and anxiolysis). The precise mechanism of the analgesic action is unknown. However, specific CNS opiate receptors and endogenous compounds with morphine-like activity have been identified throughout the brain and spinal cord and are likely to play a role in the expression of analgesic effects. Morphine produces respiratory depression by direct action on brainstem respiratory centers. The mechanism of respiratory depression involves a reduction in the responsiveness of the brainstem respiratory centers to increases in carbon dioxide tension, and to electrical stimulation. Morphine depresses the cough reflex by direct effect on the cough center in the medulla. Antitussive effects may occur with doses lower than those usually required for analgesia. Morphine causes miosis, even in total darkness, and little tolerance develops to this effect. Pinpoint pupils are a sign of opioid overdose but are not pathognomonic (e.g., pontine lesions of hemorrhagic or ischemic origins may produce similar findings). Marked mydriasis rather than miosis may be seen with worsening hypoxia in the setting of KADIAN® overdose (See OVERDOSAGE).

Effects on the Gastrointestinal Tract and Other Smooth Muscle

Gastric, biliary and pancreatic secretions are decreased by morphine. Morphine causes a reduction in motility associated with an increase in tone in the antrum of the stomach and duodenum. Digestion of food in the small intestine is delayed and propulsive contractions are decreased. Propulsive peristaltic waves in the colon are decreased, while tone is increased to the point of spasm. The end result is constipation. Morphine can cause a marked increase in biliary tract pressure as a result of spasm of the sphincter of Oddi.

Effects on the Cardiovascular System

Morphine produces peripheral vasodilation which may result in orthostatic hypotension or syncope. Release of histamine may be induced by morphine and can contribute to opioid-induced hypotension. Manifestations of histamine release and/or peripheral vasodilation may include pruritus, flushing, red eyes and sweating.

Pharmacodynamics

Plasma Level-Analgesia Relationships

In any particular patient, both analgesic effects and plasma morphine concentrations are related to the morphine dose.

While plasma morphine-efficacy relationships can be demonstrated in non-tolerant individuals, they are influenced by a wide variety of factors and are not generally useful as a guide to the clinical use of morphine. The effective dose in opioid-tolerant patients may be 10-50 times as great (or greater) than the appropriate dose for opioid-naive individuals. Dosages of morphine should be chosen and must be titrated on the basis of clinical evaluation of the patient and the balance between therapeutic and adverse effects.

For any fixed dose and dosing interval, KADIAN® will have, at steady-state, a lower Cmax and a higher Cmin than conventional morphine.

Pharmacokinetics

KADIAN® capsules contain polymer coated extended-release pellets of morphine sulfate that release morphine significantly more slowly than from conventional oral preparations. KADIAN® activity is primarily due to morphine. One metabolite, morphine-6-glucuronide, has been shown to have analgesic activity, but does not readily cross the blood-brain barrier.

Following oral administration of morphine, the extent of absorption is essentially the same for immediate or extended-release formulations, although the time to peak blood level (Tmax) will be longer and the Cmax will be lower for formulations that delay the release of morphine in the gastrointestinal tract.

Elimination of morphine is primarily via hepatic metabolism to glucuronide metabolites (55 to 65%) which are then renally excreted. The terminal half-life of morphine is 2 to 4 hours, however, a longer term half-life of about 15 hours has been reported in studies where blood has been sampled up to 48 hours.

The single-dose pharmacokinetics of KADIAN® are linear over the dosage range of 30 to 100 mg. The single dose and multiple dose pharmacokinetic parameters of KADIAN® in normal volunteers are summarized in Table 1.

Table 1: Mean pharmacokinetic parameters (% coefficient variation) resulting from a fasting single dose study in normal volunteers and a multiple dose study in patients with cancer pain.

Regimen/ | AUC#,+ | Cmax+ | Tmax | Cmin+ | Fluctuation*
Dosage Form | (ng.h/mL) | (ng/mL) | (h) | (ng/mL)
Single Dose (n=24)
KADIAN® Capsule | 271.0 (19.4) | 15.6 (24.4) | 8.6 (41.1) | na^ | na
Extended-Release Tablet | 304.3 (19.1) | 30.5 (32.1) | 2.5 (52.6) | na | na
Morphine Solution | 362.4 (42.6) | 64.4 (38.2) | 0.9 (55.8) | na | na
Multiple Dose (n=24)
KADIAN® Capsule q24h | 500.9 (38.6) | 37.3 (37.7) | 10.3 (32.2) | 9.9 (52.3) | 3.0 (45.5)
Extended-Release Tablet q12h | 457.3 (40.2) | 36.9 (42.0) | 4.4 (53.0) | 7.6 (60.3) | 4.1 (51.5)

# For single dose AUC = AUC 0-48h, for multiple dose AUC = AUC 0-24h at steady state
+ For single dose parameter normalized to 100 mg, for multiple dose parameter normalized to 100 mg per 24 hours
* Steady-state fluctuation in plasma concentrations = C max- Cmin/ Cmin
^ Not applicable

Absorption

Following the administration of oral morphine solution, approximately 50% of the morphine absorbed reaches the systemic circulation within 30 minutes. However, following the administration of an equal amount of KADIAN® to healthy volunteers, this occurs, on average, after 8 hours. As with most forms of oral morphine, because of pre-systemic elimination, only about 20 to 40% of the administered dose reaches the systemic circulation.

Food Effects: While concurrent administration of food slows the rate of absorption of KADIAN®, the extent of absorption is not affected and KADIAN® can be administered without regard to meals.

Steady State: When KADIAN® is given on a fixed dosing regimen to patients with chronic pain due to malignancy, steady state is achieved in about two days. At steady state, KADIAN® will have a significantly lower Cmax and a higher Cmin than equivalent doses of oral morphine solution and some other extended-release preparations (see Graph 1).

Graph 1 (Study # MOB-1/90): Mean steady state plasma morphine concentrations for KADIAN® (twice a day), extended-release morphine tablet (twice a day) and oral morphine solution (every 4 hours); plasma concentrations are normalized to 100 mg every 24 hours, (n=24).

When given once-daily (every 24 hours) to 24 patients with malignancy, KADIAN® had a similar Cmax and higher Cmin at steady state in clinical usage, when compared to twice-daily (every 12 hours) extended-release morphine tablets, given at an equivalent total daily dosage (see Graph 2 and Table 1). Drug-disease interactions are frequently seen in the older and more gravely ill patients, and may result in both altered absorption and reduced clearance as compared to normal volunteers (see Geriatric, Hepatic Failure, and Renal Insufficiency sections).

Graph 2 (Study # MOR-9/92): Dose normalized mean steady state plasma morphine concentrations for KADIAN® (once a day), and an equivalent dose of a 12-hour, extended-release morphine tablet given twice a day. Plasma concentrations are normalized to 100 mg every 24 hours, (n=24).

Distribution

Once absorbed, morphine is distributed to skeletal muscle, kidneys, liver, intestinal tract, lungs, spleen and brain. The volume of distribution of morphine is approximately 3 to 4 L/kg. Morphine is 30 to 35% reversibly bound to plasma proteins. Although the primary site of action of morphine is in the CNS, only small quantities pass the blood-brain barrier. Morphine also crosses the placental membranes (see PRECAUTIONS-Pregnancy) and has been found in breast milk (see PRECAUTIONS-Nursing Mothers).

Metabolism

The major pathway of the detoxification of morphine is conjugation, either with D-glucuronic acid in the liver to produce glucuronides or with sulfuric acid to give morphine-3-etheral sulfate. Although a small fraction (less than 5%) of morphine is demethylated, for all practical purposes, virtually all morphine is converted to glucuronide metabolites including morphine-3-glucuronide, M3G (about 50%) and morphine-6-glucuronide, M6G (about 5 to 15%). Studies in healthy subjects and cancer patients have shown that the glucuronide metabolite to morphine mean molar ratios (based on AUC) are similar after both single doses and at steady state for KADIAN®, 12-hour extended-release morphine sulfate tablets and morphine sulfate solution.

M3G has no significant analgesic activity. M6G has been shown to have opioid agonist and analgesic activity in humans.

Excretion

Approximately 10% of morphine dose is excreted unchanged in the urine. Most of the dose is excreted in the urine as M3G and M6G. A small amount of the glucuronide metabolites is excreted in the bile and there is some minor enterohepatic cycling. Seven to 10% of administered morphine is excreted in the feces.

The mean adult plasma clearance is about 20-30 mL/minute/kg. The effective terminal half-life of morphine after IV administration is reported to be approximately 2.0 hours. Longer plasma sampling in some studies suggests a longer terminal half-life of morphine of about 15 hours.

Special Populations Geriatric

The elderly may have increased sensitivity to morphine and may achieve higher and more variable serum levels than younger patients. In adults, the duration of analgesia increases progressively with age, though the degree of analgesia remains unchanged. KADIAN® pharmacokinetics have not been investigated in elderly patients (>65 years) although such patients were included in the clinical studies.

Nursing Mothers

Morphine is excreted in the maternal milk, and the milk to plasma morphine AUC ratio is about 2.5:1. The amount of morphine received by the infant depends on the maternal plasma concentration, amount of milk ingested by the infant, and the extent of first pass metabolism.

Pediatric

Infants under 1 month of age have a prolonged elimination half-life and decreased clearance relative to older infants and pediatric patients. The clearance of morphine and its elimination half-life begin to approach adult values by the second month of life. Pediatric patients old enough to take capsules should have pharmacokinetic parameters similar to adults, dosed on a per kilogram basis (see PRECAUTIONS-Pediatric Use).

Gender

No meaningful differences between male and female patients were demonstrated in the analysis of the pharmacokinetic data from clinical studies.

Race

Pharmacokinetic differences due to race may exist. Chinese subjects given intravenous morphine in one study had a higher clearance when compared to caucasian subjects (1852 ± 116 mL/min versus 1495 ± 80 mL/min).

Hepatic Failure

The pharmacokinetics of morphine were found to be significantly altered in individuals with alcoholic cirrhosis. The clearance was found to decrease with a corresponding increase in half-life. The M3G and M6G to morphine plasma AUC ratios also decreased in these patients indicating a decrease in metabolic activity.

Renal Insufficiency

The pharmacokinetics of morphine are altered in renal failure patients. AUC is increased and clearance is decreased. The metabolites, M3G and M6G accumulate several fold in renal failure patients compared with healthy subjects.

Drug-Drug Interactions

The known drug interactions involving morphine are pharmacodynamic, not pharmacokinetic (see PRECAUTIONS-Drug Interactions).

INDICATIONS AND USAGE

KADIAN® Capsules are an extended-release oral formulation of morphine sulfate indicated for the management of moderate to severe pain when a continuous, around-the-clock opioid analgesic is needed for an extended period of time (see CLINICAL PHARMACOLOGY).

KADIAN® Capsules are NOT intended for use as a prn analgesic.

KADIAN® is not indicated for pain in the immediate postoperative period (the first 12-24 hours following surgery), or if the pain is mild or not expected to persist for an extended period of time. KADIAN® is only indicated for postoperative use if the patient is already receiving the drug prior to surgery or if the postoperative pain is expected to be moderate to severe and persist for an extended period of time. Physicians should individualize treatment, moving from parenteral to oral analgesics as appropriate. (See American Pain Society guidelines.)

CONTRAINDICATIONS

KADIAN® is contraindicated in patients with a known hypersensitivity to morphine, morphine salts or any of the capsule components, or in any situation where opioids are contraindicated. This includes in patients with respiratory depression (in the absence of resuscitative equipment or in unmonitored settings), and in patients with acute or severe bronchial asthma or hypercarbia.

KADIAN® is contraindicated in any patient who has or is suspected of having paralytic ileus.

WARNINGS

KADIAN® Capsules are to be swallowed whole and are not to be chewed, crushed, or dissolved. Taking chewed, crushed, or dissolved KADIAN® Capsules leads to rapid release and absorption of a potentially fatal dose of morphine.

KADIAN® 100 mg and 200 mg Capsules ARE FOR USE IN OPIOID-TOLERANT PATIENTS ONLY. This capsule strength may cause fatal respiratory depression when ingested or administered to patients who are not previously exposed to opioids.

Care should be taken in the prescribing of this capsule strength. Patients should be instructed against use by individuals other than the patient for whom it was prescribed, as such inappropriate use may have severe medical consequences, including death.

Misuse, Abuse and Diversion of Opioids

KADIAN® contains morphine an opioid agonist and a Schedule II controlled substance. Opioid agonists have the potential for being abused and are sought by drug abusers and people with addiction disorders and are subject to criminal diversion.

Morphine can be abused in a manner similar to other opioid agonists, legal or illicit. This should be considered when prescribing or dispensing KADIAN® in situations where the physician or pharmacist is concerned about an increased risk of misuse, abuse, or diversion.

Abuse of KADIAN® by crushing, chewing, snorting or injecting the dissolved product will result in the uncontrolled delivery of the opioid and pose a significant risk to the abuser that could result in overdose and death (see WARNINGS and DRUG ABUSE AND DEPENDENCE)

Concerns about abuse, addiction, and diversion should not prevent the proper management of pain. Healthcare professionals should contact their State Professional Licensing Board, or State Controlled Substances Authority for information on how to prevent and detect abuse or diversion of this product.

Interactions with Alcohol and Drugs of Abuse

KADIAN® may be expected to have additive effects when used in conjunction with alcohol, other opioids, or illicit drugs that cause central nervous system depression because respiratory depression, hypotension, and profound sedation or coma may result.

Impaired Respiration

Respiratory depression is the chief hazard of all morphine preparations. Respiratory depression occurs more frequently in elderly and debilitated patients, and those suffering from conditions accompanied by hypoxia, hypercapnia, or upper airway obstruction (when even moderate therapeutic doses may significantly decrease pulmonary ventilation).

KADIAN® should be used with extreme caution in patients with chronic obstructive pulmonary disease or cor pulmonale, and in patients having a substantially decreased respiratory reserve (e.g. severe kyphoscoliosis), hypoxia, hypercapnia, or pre-existing respiratory depression. In such patients, even usual therapeutic doses of morphine may increase airway resistance and decrease respiratory drive to the point of apnea. In these patients, alternative non-opioid analgesics should be considered, and opioids should be employed only under careful medical supervision at the lowest effective dose.

Head Injury and Increased Intracranial Pressure

The respiratory depressant effects of morphine with carbon dioxide retention and secondary elevation of cerebrospinal fluid pressure may be markedly exaggerated in the presence of head injury, other intracranial lesions, or a pre-existing increase in intracranial pressure. KADIAN® produces effects which may obscure neurologic signs of further increases in pressure in patients with head injuries. Morphine should only be administered under such circumstances when considered essential and then with extreme care.

Hypotensive Effect

KADIAN® may cause severe hypotension. There is an added risk to individuals whose ability to maintain blood pressure has already been compromised by a reduced blood volume, or a concurrent administration of drugs such as phenothiazines or general anesthetics. (See also PRECAUTIONS-Drug Interactions.) KADIAN® may produce orthostatic hypotension and syncope in ambulatory patients.

KADIAN®, like all opioid analgesics, should be administered with caution to patients in circulatory shock, as vasodilation produced by the drug may further reduce cardiac output and blood pressure.

Interactions with other CNS Depressants

KADIAN® should be used with great caution and in reduced dosage in patients who are concurrently receiving other central nervous system depressants including sedatives or hypnotics, general anesthetics, phenothiazines, other tranquilizers, and alcohol because respiratory depression, hypotension, and profound sedation or coma may result.

Gastrointestinal Obstruction

KADIAN® should not be given to patients with gastrointestinal obstruction, particularly paralytic ileus, as there is a risk of the product remaining in the stomach for an extended period and the subsequent release of a bolus of morphine when normal gut motility is restored. As with other solid morphine formulations diarrhea may reduce morphine absorption.

Other

Although extremely rare, cases of anaphylaxis have been reported.

PRECAUTIONS

General

KADIAN® is intended for use in patients who require continuous, around-the-clock opioid analgesia for an extended period of time. As with any potent opioid, it is critical to adjust the dosing regimen for KADIAN® for each patient, taking into account the patient's prior analgesic treatment experience. Although it is clearly impossible to enumerate every consideration that is important to the selection of the initial dose of KADIAN®, attention should be given to the points under DOSAGE AND ADMINISTRATION.

Opioid analgesics have a narrow therapeutic index in certain patient populations, especially when combined with CNS depressant drugs, and should be reserved for cases where the benefits of opioid analgesia outweigh the known risks of respiratory depression, altered mental state, and postural hypotension.

Selection of patients for treatment with KADIAN® should be governed by the same principles that apply to the use of any potent opioid analgesics. Specifically, the increased risks associated with its use in the following populations should be considered: the elderly or debilitated and those with severe impairment of hepatic, pulmonary, or renal function; hypothyroidism; adrenocortical insufficiency (e.g., Addison's Disease); CNS depression or coma; toxic psychosis; prostatic hypertrophy, or urethral stricture; acute alcoholism; delirium tremens; kyphoscoliosis, or inability to swallow.

The administration of KADIAN® may obscure the diagnosis or clinical course in patients with acute abdominal conditions.

KADIAN® may aggravate pre-existing convulsions in patients with convulsive disorders.

Cordotomy

Patients taking KADIAN® who are scheduled for cordotomy or other interruption of pain transmission pathways should have KADIAN® ceased 24 hours prior to the procedure and the pain controlled by parenteral short-acting opioids. In addition, the post-procedure titration of analgesics for such patients should be individualized to avoid either oversedation or withdrawal syndromes.

Use in Pancreatic/Biliary Tract Disease

KADIAN® may cause spasm of the sphincter of Oddi and should be used with caution in patients with biliary tract disease, including acute pancreatitis. Opioids may cause increases in the serum amylase level.

Tolerance and Physical Dependence

Tolerance is the need for increasing doses of opioids to maintain a defined effect such as analgesia (in the absence of disease progression or other external factors). Physical dependence is manifested by withdrawal symptoms after abrupt discontinuation of a drug or upon administration of an antagonist. Physical dependence and tolerance are not unusual during chronic opioid therapy.

The opioid abstinence or withdrawal syndrome is characterized by some or all of the following: restlessness, lacrimation, rhinorrhea, yawning, perspiration, chills, myalgia, and mydriasis. Other symptoms also may develop, including: irritability, anxiety, backache, joint pain, weakness, abdominal cramps, insomnia, nausea, anorexia, vomiting, diarrhea, or increased blood pressure, respiratory rate, or heart rate.

In general, opioids should not be abruptly discontinued (see DOSAGE AND ADMINISTRATION: Cessation of Therapy).

Special Risk Groups

KADIAN® should be administered with caution, and in reduced dosages in elderly or debilitated patients; patients with severe renal or hepatic insufficiency; patients with Addison's disease; myxedema; hypothyroidism; prostatic hypertrophy or urethral stricture.

Caution should also be exercised in the administration of KADIAN® to patients with CNS depression, toxic psychosis, acute alcoholism and delirium tremens, and convulsive disorders.

Driving and Operating Machinery

KADIAN® may impair the mental and/or physical abilities needed to perform potentially hazardous activities such as driving a car or operating machinery. Patients must be cautioned accordingly. Patients should also be warned about the potential combined effects of KADIAN® with other CNS depressants, including other opioids, phenothiazines, sedative/hypnotics and alcohol (see Drug Interactions).

Information for Patients

If clinically advisable, patients receiving KADIAN®, or their caregivers should be given the following information by the physician, nurse, or pharmacist:

1. Patients should be advised that KADIAN® contains morphine and should be taken only as directed.
2. Patients should be advised that KADIAN® capsules should be swallowed whole (not chewed, crushed, or dissolved). Alternately, KADIAN® capsules may be opened and the entire contents sprinkled on a small amount of apple sauce immediately prior to ingestion. KADIAN® capsules or the contents of the capsules must not be chewed or crushed due to a risk of fatal overdose.
3. Patients should be advised that KADIAN® 100 mg and 200 mg Capsules are for use only in opioid-tolerant patients. Special care must be taken to avoid accidental ingestion or use by individuals (including children) other than the patient for whom it was originally prescribed, as such unsupervised use may have severe, even fatal, consequences.
4. Patients should be advised that the dose of KADIAN® should not be adjusted without consulting the prescribing health care provider.
5. Patients should be advised to report episodes of breakthrough pain and adverse experiences occurring during therapy. Individualization of dosage is essential to make optimal use of this medication.
6. Patients should be advised that KADIAN® may impair mental and/or physical ability required for the performance of potentially hazardous tasks (e.g., driving, operating machinery). Patients started on KADIAN® or whose dose has been changed should refrain from dangerous activity until it is established that they are not adversely affected.
7. Patients should be advised that KADIAN® should not be taken with alcohol or other CNS depressants (sleeping medication, tranquilizers) except by the orders of the prescribing healthcare provider because dangerous additive effects may occur resulting in serious injury or death.
8. Women of childbearing potential who become or are planning to become pregnant, should consult their prescribing healthcare provider prior to initiating or continuing therapy with KADIAN®.
9. Patients should be advised that if they have been receiving treatment with KADIAN® for more than a few weeks and cessation of therapy is indicated, it may be appropriate to taper the KADIAN® dose, rather than abruptly discontinue it, due to the risk of precipitating withdrawal symptoms. Their prescribing healthcare provider should provide a dose schedule to accomplish a gradual discontinuation of the medication.
10. Patients should be advised that KADIAN® is a potential drug of abuse. They should protect it from theft, and it should never be given to anyone other than the individual for whom it was prescribed.
11. Patients should be advised that severe constipation could occur as a result of taking KADIAN® and appropriate laxatives, stool softeners and other appropriate treatments should be initiated from the beginning of opioid therapy.
12. Patients should be instructed to keep KADIAN® in a secure place out of the reach of children. When KADIAN® is no longer needed, the unused capsules should be destroyed by flushing down the toilet.

Drug Interactions

CNS Depressants: Morphine should be used with great caution and in reduced dosage in patients who are concurrently receiving other central nervous system (CNS) depressants including sedatives, hypnotics, general anesthetics, antiemetics, phenothiazines, other tranquilizers and alcohol because of the risk of respiratory depression, hypotension and profound sedation or coma. When such combined therapy is contemplated, the initial dose of one or both agents should be reduced by at least 50%.

Muscle Relaxants: KADIAN® may enhance the neuromuscular blocking action of skeletal relaxants and produce an increased degree of respiratory depression.

Mixed Agonist/Antagonist Opioid Analgesics: Agonist/antagonist analgesics (i.e., pentazocine, nalbuphine, and butorphanol) should be administered with caution to a patient who has received or is receiving a course of therapy with a pure opioid agonist analgesic such as KADIAN®. In this situation, mixed agonist/antagonist analgesics may reduce the analgesic effect of KADIAN® and/or may precipitate withdrawal symptoms in these patients.

Monoamine Oxidase Inhibitors (MAOIs): MAOIs have been reported to intensify the effects of at least one opioid drug causing anxiety, confusion and significant depression of respiration or coma. KADIAN® should not be used in patients taking MAOIs or within 14 days of stopping such treatment.

Cimetidine: There is an isolated report of confusion and severe respiratory depression when a hemodialysis patient was concurrently administered morphine and cimetidine.

Diuretics: Morphine can reduce the efficacy of diuretics by inducing the release of antidiuretic hormone. Morphine may also lead to acute retention of urine by causing spasm of the sphincter of the bladder, particularly in men with prostatism.

Carcinogenesis, Mutagenesis, Impairment of Fertility

Long-term studies in animals to evaluate the carcinogenic potential of morphine have not been conducted. There are no reports of carcinogenic effects in humans. In vitro studies have reported that morphine is non-mutagenic in the Ames test with Salmonella, and induces chromosomal aberrations in human leukocytes and lethal mutation induction in Drosophila. Morphine was found to be mutagenic in vitro in human T-cells, increasing the DNA fragmentation. In vivo, morphine was mutagenic in the mouse micronucleus test and induced chromosomal aberrations in spermatids and murine lymphocytes. Chronic opioid abusers (e.g., heroin abusers) and their offspring display higher rates of chromosomal damage. However, the rates of chromosomal abnormalities were similar in nonexposed individuals and in heroin users enrolled in long term opioid maintenance programs.

Pregnancy
Teratogenic Effects

(Pregnancy Category C)

Teratogenic effects of morphine have been reported in the animal literature. High parental doses during the second trimester were teratogenic in neurological, soft and skeletal tissue. The abnormalities included encephalopathy and axial skeletal fusions. These doses were often maternally toxic and were 0.3 to 3-fold the maximum recommended human dose (MRHD) on a mg/m^2 basis. The relative contribution of morphine-induced maternal hypoxia and malnutrition, each of which can be teratogenic, has not been clearly defined. Treatment of male rats with approximately 3-fold the MRHD for 10 days prior to mating decreased litter size and viability.

Nonteratogenic Effects

Morphine given subcutaneously, at non-maternally toxic doses, to rats during the third trimester with approximately 0.15-fold the MRHD caused reversible reductions in brain and spinal cord volume, and testes size and body weight in the offspring, and decreased fertility in female offspring. The offspring of rats and hamsters treated orally or intraperitoneally throughout pregnancy with 0.04- to 0.3-fold the MRHD of morphine have demonstrated delayed growth, motor and sexual maturation and decreased male fertility. Chronic morphine exposure of fetal animals resulted in mild withdrawal, altered reflex and motor skill development, and altered responsiveness to morphine that persisted into adulthood.

There are no well-controlled studies of chronic in utero exposure to morphine sulfate in human subjects. However, uncontrolled retrospective studies of human neonates chronically exposed to other opioids in utero, demonstrated reduced brain volume which normalized over the first month of life. Infants born to opioid-abusing mothers are more often small for gestational age, have a decreased ventilatory response to CO2 and increased risk of sudden infant death syndrome. KADIAN® should only be used during pregnancy if the need for strong opioid analgesia justifies the potential risk to the fetus.

Labor and Delivery

KADIAN® is not recommended for use in women during and immediately prior to labor, where shorter acting analgesics or other analgesic techniques are more appropriate. Occasionally, opioid analgesics may prolong labor through actions which temporarily reduce the strength, duration and frequency of uterine contractions. However, this effect is not consistent and may be offset by an increased rate of cervical dilatation which tends to shorten labor. Neonates whose mothers received opioid analgesics during labor should be observed closely for signs of respiratory depression. A specific opioid antagonist, such as naloxone or nalmefene, should be available for reversal of opioid-induced respiratory depression in the neonate.

Neonatal Withdrawal Syndrome

Chronic maternal use of opiates or opioids during pregnancy coexposes the fetus. The newborn may experience subsequent neonatal withdrawal syndrome (NWS). Manifestations of NWS include irritability, hyperactivity, abnormal sleep pattern, high-pitched cry, tremor, vomiting, diarrhea, weight loss, and failure to gain weight. The onset, duration, and severity of the disorder differ based on such factors as the addictive drug used, time and amount of mother’s last dose, and rate of elimination of the drug from the newborn. Approaches to the treatment of this syndrome have included supportive care and, when indicated, drugs such as paregoric or phenobarbital.

Nursing Mothers

Low levels of morphine sulfate have been detected in human milk. Withdrawal symptoms can occur in breast-feeding infants when maternal administration of morphine sulfate is stopped. Because of the potential for adverse reactions in nursing infants from KADIAN®, a decision should be made whether to discontinue nursing or discontinue the drug, taking into account the importance of the drug to the mother.

Pediatric Use

The safety of KADIAN®, both the entire capsule and the pellets sprinkled on apple sauce, have not been directly investigated in pediatric patients below the age of 18 years. The range of doses available is not suitable for the treatment of very young pediatric patients or those who are not old enough to take capsules safely. The apple sauce sprinkling method is not an appropriate alternative for these patients.

Geriatric Use

Clinical studies of KADIAN® did not include sufficient numbers of subjects aged 65 and over to determine whether they respond differently from younger subjects. Other reported clinical experience has not identified differences in responses between the elderly and younger patients. In general, dose selection for an elderly patient should be cautious, usually starting at the low end of the dosing range, reflecting the greater frequency of decreased hepatic, renal, or cardiac function, and of concomitant disease or other drug therapy.

ADVERSE REACTIONS

Serious adverse reactions that may be associated with KADIAN® therapy in clinical use are those observed with other opioid analgesics and include: respiratory depression, respiratory arrest, apnea, circulatory depression, cardiac arrest, hypotension, and/or shock (see OVERDOSAGE, WARNINGS).

The less severe adverse events seen on initiation of therapy with KADIAN® are also typical opioid side effects. These events are dose dependent, and their frequency depends on the clinical setting, the patient's level of opioid tolerance, and host factors specific to the individual. They should be expected and managed as a part of opioid analgesia. The most frequent of these include drowsiness, dizziness, constipation and nausea. In many cases, the frequency of these events during initiation of therapy may be minimized by careful individualization of starting dosage, slow titration, and the avoidance of large rapid swings in plasma concentrations of the opioid. Many of these adverse events, will cease or decrease as KADIAN® therapy is continued and some degree of tolerance is developed, but others may be expected to remain troublesome throughout therapy.

Management of Excessive Drowsiness

Most patients receiving KADIAN® will experience initial drowsiness. This usually disappears within 3-5 days and is not a cause of concern unless it is excessive, or accompanied by unsteadiness or confusion. Dizziness and unsteadiness may be associated with postural hypotension, particularly in elderly or debilitated patients, and has been associated with syncope and falls in non-tolerant patients started on opioids.

Excessive or persistent sedation should be investigated. Factors to be considered should include: concurrent sedative medications, the presence of hepatic or renal insufficiency, hypoxia or hypercapnia due to exacerbated respiratory failure, intolerance to the dose used (especially in older patients), disease severity and the patient's general condition.

The dosage should be adjusted according to individual needs, but additional care should be used in the selection of initial doses for the elderly patient, the cachectic or gravely ill patient, or in patients not already familiar with opioid analgesic medications to prevent excessive sedation at the onset of treatment.

Management of Nausea and Vomiting

Nausea and vomiting are common after single doses of KADIAN® or as an early undesirable effect of chronic opioid therapy. The prescription of a suitable antiemetic should be considered, with the awareness that sedation may result (see Drug Interactions). The frequency of nausea and vomiting usually decreases within a week or so but may persist due to opioid-induced gastric stasis. Metoclopramide is often useful in such patients.

Management of Constipation

Virtually all patients suffer from constipation while taking opioids, such as KADIAN®, on a chronic basis. Some patients, particularly elderly, debilitated or bedridden patients may become impacted. Tolerance does not usually develop for the constipating effects of opioids. Patients must be cautioned accordingly and laxatives, softeners and other appropriate treatments should be used prophylactically from the beginning of opioid therapy.

Adverse Events Probably Related to KADIAN® Administration

In clinical studies in patients with chronic cancer pain the most common adverse events reported by patients at least once during therapy were drowsiness (9%), constipation (9%), nausea (7%), dizziness (6%), and anxiety (6%). Other less common side effects expected from KADIAN® or seen in less than 3% of patients in the clinical studies were:

Body as a Whole: Asthenia, accidental injury, fever, pain, chest pain, headache, diaphoresis, chills, flu syndrome, back pain, malaise, withdrawal syndrome

Cardiovascular: Tachycardia, atrial fibrillation, hypotension, hypertension, pallor, facial flushing, palpitations, bradycardia, syncope

Central Nervous System: Confusion, dry mouth, anxiety, abnormal thinking, abnormal dreams, lethargy, depression, tremor, loss of concentration, insomnia, amnesia, paresthesia, agitation, vertigo, foot drop, ataxia, hypesthesia, slurred speech, hallucinations, vasodilation, euphoria, apathy, seizures, myoclonus

Endocrine: Hyponatremia due to inappropriate ADH secretion, gynecomastia

Gastrointestinal: Vomiting, anorexia, dysphagia, dyspepsia, diarrhea, abdominal pain, stomach atony disorder, gastro-esophageal reflux, delayed gastric emptying, biliary colic

Hemic and Lymphatic: Anemia, leukopenia, thrombocytopenia

Metabolic and Nutritional: Peripheral edema, hyponatremia, edema

Musculoskeletal: Back pain, bone pain, arthralgia

Respiratory: Hiccup, rhinitis, atelectasis, asthma, hypoxia, dyspnea, respiratory insufficiency, voice alteration, depressed cough reflex, non-cardiogenic pulmonary edema

Skin and Appendages: Rash, decubitus ulcer, pruritus, skin flush

Special Senses: Amblyopia, conjunctivitis, miosis, blurred vision, nystagmus, diplopia

Urogenital: Urinary abnormality, amenorrhea, urinary retention, urinary hesitancy, reduced libido, reduced potency, prolonged labor

Post-marketing Adverse Events Probably Related to KADIAN®

The safety of KADIAN® has been evaluated in a randomized, prospective, open-label, 4-week treatment period, post-marketing study consisting of 1418 patients ages 18-85 with chronic, non-malignant pain (e.g., back pain, osteoarthritis, neuropathic pain). No control arm was included in this study. The most common adverse events reported at least once during therapy were constipation (12%), nausea (9%) and somnolence (3%). Other less common side effects occurring in less than 3% of patients were vomiting, pruritus, dizziness, sedation, dry mouth, headache, fatigue and rash.

DRUG ABUSE AND DEPENDENCE

KADIAN® is a mu-agonist opioid with an abuse liability similar to other opioid agonists and is a Schedule II controlled substance. KADIAN® and other opioids used in analgesia can be abused and are subject to criminal diversion.

KADIAN® is an opioid with no approved use in the management of addiction disorders. Its proper usage in individuals with drug or alcohol dependence, either active or in remission, is for the management of pain requiring opioid analgesia.

Drug addiction is characterized by compulsive use, use for non-medical purposes, and continued use despite harm or risk of harm. Drug addiction is a treatable disease, utilizing a multi-disciplinary approach, but relapse is common.

“Drug-seeking” behavior is very common in addicts and drug abusers. Drug-seeking tactics include emergency calls or visits near the end of office hours, refusal to undergo appropriate examination, testing or referral, repeated “loss” of prescriptions, tampering with prescriptions and reluctance to provide prior medical records or contact information for other treating physician(s). “Doctor shopping” to obtain additional prescriptions is common among drug abusers and people suffering from untreated addiction.

Abuse and addiction are separate and distinct from physical dependence and tolerance. Physicians should be aware that addiction may not be accompanied by concurrent tolerance and symptoms of physical dependence in all addicts. In addition, abuse of opioids can occur in the absence of true addiction and is characterized by misuse for non-medical purposes, often in combination with other psychoactive substances. KADIAN®, like other opioids, has been diverted for non-medical use. Careful record-keeping of prescribing information, including quantity, frequency, and renewal requests is strongly advised.

Proper assessment of the patient, proper prescribing practices, periodic re-evaluation of therapy, and proper dispensing and storage are appropriate measures that help to limit abuse of opioid drugs.

KADIAN® is intended for oral use only. Abuse of chewed, crushed, or dissolved capsules or pellets poses a hazard of overdose and death. This risk is increased with concurrent abuse of alcohol and other substances. Due to the presence of talc as one of the excipients in capsules, parenteral abuse can be expected to result in local tissue necrosis, infection, pulmonary granulomas, and increased risk of endocarditis and valvular heart injury. Parenteral drug abuse is commonly associated with transmission of infectious diseases such as hepatitis and HIV.

OVERDOSAGE

Symptoms

Acute overdosage with morphine is manifested by respiratory depression, somnolence progressing to stupor or coma, skeletal muscle flaccidity, cold and clammy skin, constricted pupils, and, sometimes, pulmonary edema, bradycardia, hypotension and death. Marked mydriasis rather than miosis may be seen due to severe hypoxia in overdose situations.

Treatment

Primary attention should be given to the re-establishment of a patent airway and institution of assisted or controlled ventilation. Gastric contents may need to be emptied to remove unabsorbed drug when an extended-release formulation such as KADIAN® has been taken. Care should be taken to secure the airway before attempting treatment by gastric emptying or activated charcoal.

Supportive measures (including oxygen, vasopressors) should be employed in the management of circulatory shock and pulmonary edema accompanying overdose as indicated. Cardiac arrest or arrhythmias may require cardiac massage or defibrillation.

The pure opioid antagonists, naloxone or nalmefene, are specific antidotes to respiratory depression which results from opioid overdose. Since the duration of reversal would be expected to be less than the duration of action of KADIAN®, the patient must be carefully monitored until spontaneous respiration is reliably re-established. KADIAN® will continue to release and add to the morphine load for up to 24 hours after administration and the management of an overdose should be monitored accordingly. If the response to opioid antagonists is suboptimal or not sustained, additional antagonist should be given as directed by the manufacturer of the product.

Opioid antagonists should not be administered in the absence of clinically significant respiratory or circulatory depression secondary to morphine overdose. Such agents should be administered cautiously to persons who are known, or suspected to be physically dependent on KADIAN®. In such cases, an abrupt or complete reversal of opioid effects may precipitate an acute abstinence syndrome.

Opioid Tolerant Individuals: In an individual physically dependent on opioids, administration of the usual dose of the antagonist will precipitate an acute withdrawal. The severity of the withdrawal produced will depend on the degree of physical dependence and the dose of the antagonist administered. Use of an opioid antagonist should be reserved for cases where such treatment is clearly needed. If it is necessary to treat serious respiratory depression in the physically dependent patient, administration of the antagonist should be begun with care and by titration with smaller than usual doses of the antagonist.

DOSAGE AND ADMINISTRATION

KADIAN® may be administered once or twice daily.

KADIAN® capsules should be swallowed whole. The pellets in KADIAN® capsules should not be chewed, crushed, or dissolved due to the risk of rapid release and absorption of a potentially fatal dose of morphine.

Alternatively, KADIAN® capsules may be administered as a sprinkle on apple sauce or through a 16 French gastrostomy tube (see ALTERNATIVE METHODS OF ADMINISTRATION section).

The 100 mg and 200 mg capsules are for use only in opioid-tolerant patients.

KADIAN® is not indicated for pre-emptive analgesia (administration pre-operatively for the management of post-operative pain), or for pain in the immediate post-operative period (the first 12 to 24 hours following surgery) for patients not previously taking the drug, because its safety in these settings have not been established.

KADIAN® is only indicated for post-operative use if the patient is already receiving the drug prior to surgery or if the postoperative pain is expected to be moderate to severe and persist for an extended period of time.

Patients who are already receiving KADIAN® Capsules as part of ongoing analgesic therapy may be safely continued on the drug if appropriate dosage adjustments are made considering the procedure, other drugs given, and the temporary changes in physiology caused by the surgical intervention.

Initiating Therapy with KADIAN® Capsules

Physicians should individualize treatment using a progressive plan of pain management such as outlined by the World Health Organization, the American Pain Society and the Federation of State Medical Boards Model Guidelines. Health care professionals should follow appropriate pain management principles of careful assessment and ongoing monitoring.

It is critical to adjust the dosing regimen for each patient individually, taking into account the patient's prior analgesic treatment experience. In the selection of the initial dose of KADIAN®, attention should be given to:

1. the total daily dose, potency and kind of opioid the patient has been taking previously;
2. the reliability of the relative potency estimate used to calculate the equivalent dose of morphine needed (Note: potency estimates may vary with the route of administration);
3. the patient's degree of opioid experience and opioid tolerance;
4. the general condition and medical status of the patient;
5. concurrent medication;
6. the type and severity of the patient's pain.

Care should be taken to use low initial doses of KADIAN® in patients who are not already opioid-tolerant, especially those who are receiving concurrent treatment with muscle relaxants, sedatives, or other CNS active medications (see PRECAUTIONS).

During periods of changing analgesic requirements including initial titration, frequent communication is recommended between physician, other members of the healthcare team, the patient, and the caregiver/family.

The following dosing recommendations, therefore, can only be considered suggested approaches to what is actually a series of clinical decisions over time in the management of the pain of an individual patient.

Conversion from Other Oral Morphine Formulations to KADIAN®

Patients on other oral morphine formulations may be converted to KADIAN® by administering one-half of the patient's total daily oral morphine dose as KADIAN® capsules every 12 hours (twice-a-day) or by administering the total daily oral morphine dose as KADIAN® capsules every 24 hours (once-a-day). KADIAN® should not be given more frequently than every 12 hours.

Conversion from Parenteral Morphine or Other Parenteral or Oral Opioids to KADIAN®

KADIAN® can be administered to patients previously receiving treatment with parenteral morphine or other opioids. While there are useful tables of oral and parenteral equivalents in cancer analgesia, there is substantial interpatient variation in the relative potency of different opioid drugs and formulations. For these reasons, it is better to underestimate the patient's 24-hour oral morphine requirement and provide rescue medication, than to overestimate and manage an adverse event. The following general points should be considered:

1. Parenteral to Oral Morphine Ratio: It may take anywhere from 2-6 mg of oral morphine to provide analgesia equivalent to 1 mg of parenteral morphine. A dose of oral morphine three times the daily parenteral morphine requirement may be sufficient in chronic use settings.
2. Other Parenteral or Oral Opioids to Oral Morphine Sulfate: There is lack of systematic evidence bearing on these types of analgesic substitutions. Therefore, specific recommendations are not possible. Physicians are advised to refer to published relative potency data, keeping in mind that such ratios are only approximate. In general, it is safest to give half of the estimated daily morphine demand as the initial dose, and to manage inadequate analgesia by supplementation with immediate-release morphine. (See discussion which follows.)

The first dose of KADIAN® may be taken with the last dose of any immediate-release (short-acting) opioid medication due to the long delay until the peak effect after administration of KADIAN®.

Use of KADIAN® as the First Opioid Analgesic

There has been no evaluation of KADIAN® as an initial opioid analgesic in the management of pain. Because it may be more difficult to titrate a patient to adequate analgesia using an extended-release morphine, it is ordinarily advisable to begin treatment using an immediate-release morphine formulation.

Individualization of Dosage

The best use of opioid analgesics in the management of chronic malignant and non-malignant pain is challenging, and is well described in materials published by the World Health Organization and the Agency for Health Care Policy and. KADIAN® is a third step drug which is most useful when the patient requires a constant level of opioid analgesia as a "floor" or "platform" from which to manage breakthrough pain. When a patient has reached the point where comfort cannot be provided with a combination of non-opioid medications (NSAIDs and acetaminophen) and intermittent use of moderate or strong opioids, the patient's total opioid therapy should be converted into a 24 hour oral morphine equivalent.

KADIAN® should be started by administering one-half of the estimated total daily oral morphine dose every 12 hours (twice-a-day) or by administering the total daily oral morphine dose every 24 hours (once-a-day). The dose should be titrated no more frequently than every-other-day to allow the patients to stabilize before escalating the dose. If breakthrough pain occurs, the dose may be supplemented with a small dose (less than 20% of the total daily dose) of a short-acting analgesic. Patients who are excessively sedated after a once-a-day dose or who regularly experience inadequate analgesia before the next dose should be switched to twice-a-day dosing.

Patients who do not have a proven tolerance to opioids should be started only on the 10 mg or 20 mg strength, and usually should be increased at a rate not greater than 20 mg every-other-day. Most patients will rapidly develop some degree of tolerance, requiring dosage adjustment until they have achieved their individual best balance between baseline analgesia and opioid side effects such as confusion, sedation and constipation. No guidance can be given as to the recommended maximal dose, especially in patients with chronic pain of malignancy. In such cases the total dose of KADIAN® should be advanced until the desired therapeutic endpoint is reached or clinically significant opioid-related adverse reactions intervene.

Alternative Methods of Administration

In a study of healthy volunteers, KADIAN® pellets sprinkled over apple sauce were found to be bioequivalent to KADIAN® capsules swallowed whole with apple sauce under fasting conditions. Other foods have not been tested. Patients who have difficulty swallowing whole capsules or tablets may benefit from this alternative method of administration.

1. Sprinkle the pellets onto a small amount of apple sauce. Apple sauce should be room temperature or cooler.
2. The patient must be cautioned not to chew the pellets which could result in the immediate release of a potentially dangerous, even fatal dose of morphine.
3. Use immediately.
4. Rinse mouth to ensure all pellets have been swallowed.
5. Patients should consume entire portion and should not divide apple sauce into separate doses.

The entire capsule contents may alternatively be administered through a 16 French gastrostomy tube.

1. Flush the gastrostomy tube with water to ensure that it is wet.
2. Sprinkle the KADIAN® Pellets into 10 mL of water.
3. Use a swirling motion to pour the pellets and water into the gastrostomy tube through a funnel.
4. Rinse the beaker with a further 10 mL of water and pour this into the funnel.
5. Repeat rinsing until no pellets remain in the beaker.

THE ADMINISTRATION OF KADIAN® PELLETS THROUGH A NASOGASTRIC TUBE SHOULD NOT BE ATTEMPTED.

Considerations in the Adjustment of Dosing Regimens

If signs of excessive opioid effects are observed early in the dosing interval, the next dose should be reduced. If this adjustment leads to inadequate analgesia, that is, if breakthrough pain occurs when KADIAN® is administered on an every 24 hours dosing regimen, consideration should be given to dosing every 12 hours. If breakthrough pain occurs on a 12 hour dosing regimen a supplemental dose of a short-acting analgesic may be given. As experience is gained, adjustments in both dose and dosing interval can be made to obtain an appropriate balance between pain relief and opioid side effects. To avoid accumulation the dosing interval of KADIAN® should not be reduced below 12 hours.

Cessation of Therapy

When the patient no longer requires therapy with KADIAN® capsules, doses should be tapered gradually to prevent signs and symptoms of withdrawal in the physically dependent patient.

Conversion from KADIAN® to Other Extended-Release Oral Morphine Formulations

KADIAN® is not bioequivalent to other extended-release morphine preparations. Although for a given dose the same total amount of morphine is available from KADIAN® as from morphine solution or extended-release morphine tablets, the slower release of morphine from KADIAN® results in reduced maximum and increased minimum plasma morphine concentrations than with shorter acting morphine products. Conversion from KADIAN® to the same total daily dose of extended-release morphine preparations may lead to either excessive sedation at peak or inadequate analgesia at trough and close observation and appropriate dosage adjustments are recommended.

Conversion from KADIAN® to Parenteral Opioids

When converting a patient from KADIAN® to parenteral opioids, it is best to calculate an equivalent parenteral dose, and then initiate treatment at half of this calculated value. For example, to estimate the required 24 hour dose of parenteral morphine for a patient taking KADIAN®, one would take the 24 hour KADIAN® dose, divide by an oral to parenteral conversion ratio of 3, divide the estimated 24 hour parenteral dose into six divided doses (for a four hour dosing interval), then halve this dose as an initial trial.

For example, to estimate the required parenteral morphine dose for a patient taking 360 mg of KADIAN® a day, divide the 360 mg daily oral morphine dose by a conversion ratio of 1 mg of parenteral morphine for every 3 mg of oral morphine. The estimated 120 mg daily parenteral requirement is then divided into six 20 mg doses, and half of this, or 10 mg, is then given every 4 hours as an initial trial dose.

This approach is likely to require a dosage increase in the first 24 hours for many patients, but is recommended because it is less likely to cause overdose than trying to establish an equivalent dose without titration.

Safety and Handling

KADIAN® Capsules contain morphine sulfate which is a controlled substance under Schedule II of the Controlled Substances Act. Morphine, like all opioids, is liable to diversion and misuse and should be handled accordingly. Patients and their families should be instructed to flush any KADIAN® capsules that are no longer needed.

KADIAN® may be targeted for theft and diversion by criminals. Healthcare professionals should contact their State Professional Licensing Board or State Controlled Substances Authority for information on how to prevent and detect abuse or diversion of this product.

KADIAN® consists of closed hard gelatin capsules containing polymer coated morphine sulfate pellets that pose no known handling risk to health care workers. KADIAN® Capsules are liable to diversion and misuse both by the general public and health care workers, and should be handled accordingly.

HOW SUPPLIED

KADIAN® capsules contain white to off-white or tan colored polymer coated extended-release pellets of morphine sulfate and are available in eight dose strengths:

10 mg size 4 capsule, light blue opaque cap printed with KADIAN and light blue opaque body printed with 10 mg. Capsules are supplied in bottles of 100 (NDC 46987-410-11).

20 mg size 4 capsule, yellow opaque cap printed with KADIAN and yellow opaque body printed with 20 mg. Capsules are supplied in bottles of 100 (NDC 46987-322-11).

30 mg size 4 capsule, blue violet opaque cap printed with KADIAN and blue violet opaque body printed with 30 mg. Capsules are supplied in bottles of 100 (NDC 46987-325-11).

50 mg size 2 capsule, blue opaque cap printed with KADIAN and blue opaque body printed with 50 mg. Capsules are supplied in bottles of 100 (NDC 46987-323-11).

60 mg size 1 capsule, pink opaque cap printed with KADIAN and pink opaque body printed with 60 mg. Capsules are supplied in bottles of 100 (NDC 46987-326-11).

80 mg size 0 capsule, light orange opaque cap printed with KADIAN and light orange opaque body printed with 80 mg. Capsules are supplied in bottles of 100 (NDC 46987-412-11).

100 mg size 0 capsule, green opaque cap printed with KADIAN and green opaque body printed with 100 mg. Capsules are supplied in bottles of 100 (NDC 46987-324-11).

200 mg size 0 capsule, light brown opaque cap printed with KADIAN and light brown opaque body printed with 200 mg. Capsules are supplied in bottles of 100 (NDC 46987-377-11).

Store at 25°C (77°F); excursions permitted to 15°-30°C (59°-86°F). Protect from light and moisture.

Dispense in a sealed tamper-evident, childproof, light-resistant container.

CAUTION: DEA Order Form Required.

KADIAN® is a registered trademark of Actavis Elizabeth LLC

Revised – February 2010

Distributed by:
Actavis Kadian LLC
60 Columbia Rd., Bldg. B
Morristown, NJ 07960 USA

40-9101

PACKAGE LABEL - KADIAN C-II 20 MG CAPSULE

PACKAGE LABEL - KADIAN C-II 30 MG CAPSULE

PACKAGE LABEL - KADIAN C-II 50 MG CAPSULE

PACKAGE LABEL - KADIAN C-II 60 MG CAPSULE

PACKAGE LABEL - KADIAN C-II 80 MG CAPSULE

PACKAGE LABEL - KADIAN C-II 100 MG CAPSULE

PACKAGE LABEL - KADIAN C-II 200 MG CAPSULE